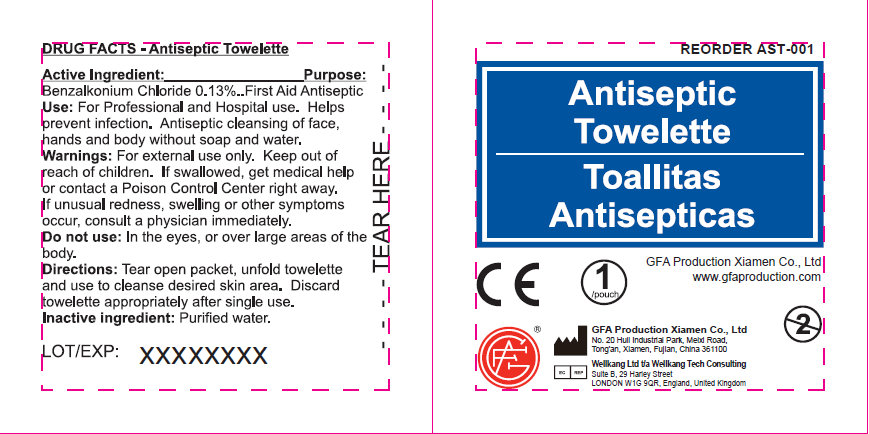 DRUG LABEL: Antiseptic
NDC: 52124-0001 | Form: SWAB
Manufacturer: Genuine First Aid LLC
Category: otc | Type: HUMAN OTC DRUG LABEL
Date: 20120429

ACTIVE INGREDIENTS: BENZALKONIUM CHLORIDE 1.3 mg/1 mL
INACTIVE INGREDIENTS: WATER

Antiseptic Towelette

Active Ingredient

Benzalkonium Chloride 0.13

Purpose

Antiseptic

Use

For Professional and Hospital use. Helps prevent infection. Antiseptic cleansing of face, hands and body without soap and water.

Warnings

Warning: For external use only.

Keep out of reach of children: If swallowed, get medical help or contact a Poison Control Center right away.

Stop use if unusual redness, swelling or other symptoms occur. Consult a physician immediately.

Do not use in the eyes or over large areas of the body.

Directions

Tear open packet, unfold towelette and use to cleanse desired skin area. Discard towelette appropriately after single use.

Inactive Ingredients

Inactive Ingredient: Purified water

LOT/EXP: Made in CHINA

20130301

PACKAGE LABEL

Antiseptic Towelette

Genuine First Aid LLC, Clearwater FL 33755

www.GenuineFirstAid.com

1/pouch

GENUINE FIRST AID